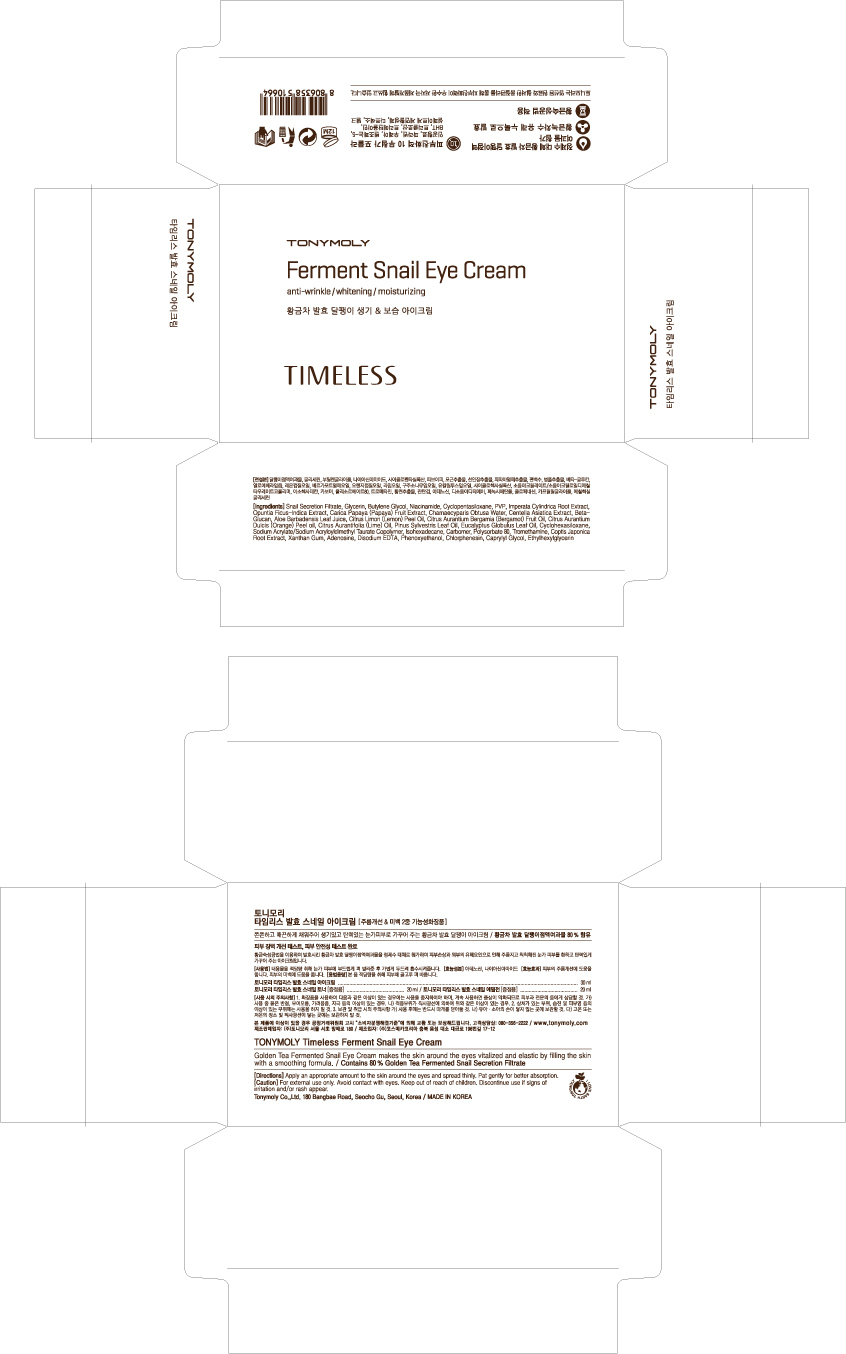 DRUG LABEL: TONYMOLY Timeless Ferment Snail Eye Cream
NDC: 59078-104 | Form: CREAM
Manufacturer: Tonymoly Co., Ltd.
Category: otc | Type: HUMAN OTC DRUG LABEL
Date: 20160202

ACTIVE INGREDIENTS: GLYCERIN 1510.8 mg/140 mL
INACTIVE INGREDIENTS: IMPERATA CYLINDRICA ROOT; POTASSIUM SORBATE; SODIUM BENZOATE; BUTYLENE GLYCOL; NIACINAMIDE; ISOHEXADECANE; WATER; TROMETHAMINE; POLYSORBATE 80; PHENOXYETHANOL; CHLORPHENESIN; ETHYLHEXYLGLYCERIN; XANTHAN GUM; CAPRYLYL GLYCOL; ADENOSINE; PROPANEDIOL; CHAMAECYPARIS OBTUSA WHOLE; EDETATE DISODIUM; OPUNTIA FICUS-INDICA; CENTELLA ASIATICA; POVIDONES; SODIUM ACRYLATE; BERGAMOT OIL; COPTIS JAPONICA ROOT; LEMON PEEL; POLYETHYLENE GLYCOL 400; ORANGE PEEL; LIME PEEL; PINE NEEDLE OIL (PINUS SYLVESTRIS); EUCALYPTUS GLOBULUS LEAF; PAPAYA; ALOE VERA LEAF

Active Ingredients

Glycerin 4.00%

Purpose

Skin Protectant

Dosage

Take an adequate amount of the product, gently apply to a face and neck area.

Caution

For external use only. Avoid contact with eyes. Keep out of reach of children. Discontinue use if signs of irritation and/or rash appear.

Keep out of reach of children. Discontinue use if signs of irritation and/or rash appear.

Directions

Apply an appropriate amount to the skin around the eyes and spread thinly. Pat gently for better absorption.

Inactive Ingredients

Snail Secretion Filtrate, Butylene Glycol, Niacinamide, Cyclopentasiloxane, PVP, Cyclohexasiloxane, Sodium Acrylate/Sodium Acryloyldimethyl Taurate Copolymer, Isohexadecane, Water, Carbomer, Tromethamine, Polysorbate 80, Phenoxyethanol, Chlorphenesin, Ethylhexylglycerin, Xanthan Gum, Caprylyl Glycol, Chamaecyparis Obtusa Water, Imperata Cylindrica Root Extract, Adenosine, Disodium EDTA, Opuntia Ficus-Indica Extract, Coptis Japonica Root Extract, Citrus Medica Limonum (Lemon) Peel Oil, Propanediol, Citrus Aurantium Bergamia (Bergamot) Fruit Oil, PEG-8, Citrus aurantium dulcis (orange) peel oil, Citrus Aurantifolia (Lime) Oil, Pinus Sylvestris Leaf Oil, Centella Asiatica Extract, Eucalyptus Globulus Leaf Oil, Carica papaya (papaya) fruit Extract, Aloe Barbadensis Leaf Juice, Beta-Glucan, Potassium sorbate, Sodium Benzoate